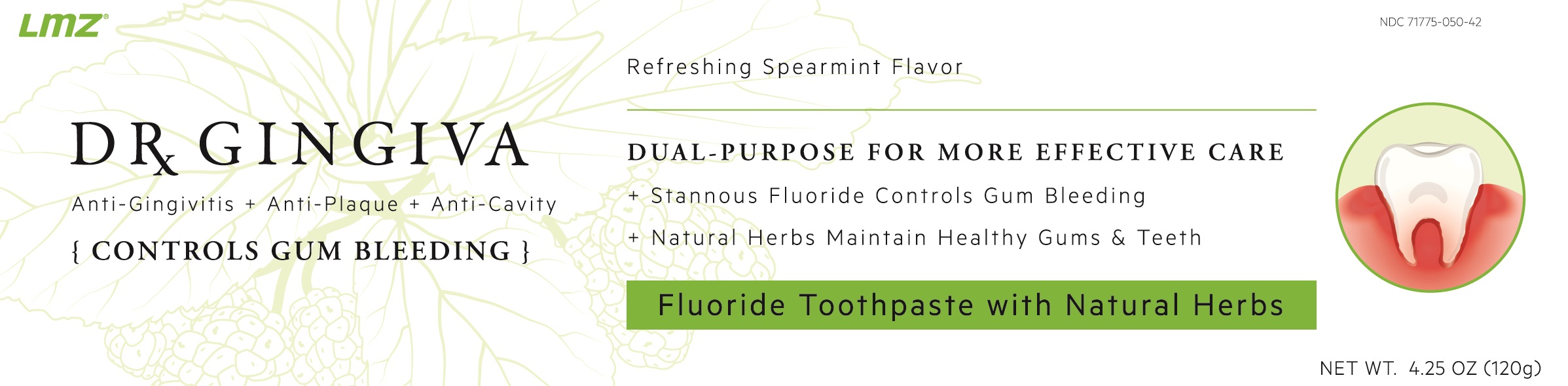 DRUG LABEL: Dr. Gingiva
NDC: 71775-050 | Form: PASTE
Manufacturer: LIUZHOU LMZ CO., LTD.
Category: otc | Type: HUMAN OTC DRUG LABEL
Date: 20200109

ACTIVE INGREDIENTS: STANNOUS FLUORIDE 1.5 mg/1 g
INACTIVE INGREDIENTS: SORBITOL; HYDRATED SILICA; WATER; POLYETHYLENE GLYCOL 400; SODIUM LAUROYL SARCOSINATE; CARBOXYMETHYLCELLULOSE; ZANTHOXYLUM NITIDUM ROOT; CLINOPODIUM CHINENSE WHOLE; SODIUM COPPER CHLOROPHYLLIN; CHONDRUS CRISPUS; TITANIUM DIOXIDE; ETHYL MENTHANE CARBOXAMIDE; SACCHARIN SODIUM; SODIUM PHOSPHATE, TRIBASIC, ANHYDROUS; SODIUM BICARBONATE; BENZYL ALCOHOL; SODIUM CHLORIDE

Active ingredients

Stannous fluoride 0.454 % (0.15 % w/v fluoride ion)

Purposes

Anticavity
Antigingivitis

Uses

- helps control bleeding gums and gingivitis. ▪ aids in the prevention of dental cavities.
- aids in the prevention of dental cavities.
- helps interfere with harmful effects of plaque associated with gingivitis.

Warnings

- this product is not intended to control major bleeding. Ask a dentist or doctor if you have major bleeding in mouth.
- do not use if irritation occurs.

Stop use and ask a dentist if

- gingivitis, bleeding, or redness persists for more than 2 weeks.
- you have painful or swollen gums, pus from the gum line, loose teeth, or increasing spacing between the teeth. These may be signs or symptoms of periodontitis, a serious form of gum disease.

Keep out of reach of children under 6 years of age.

If more than used for brushing is accidentally swallowed, get medical help or contact a Poison Control Center right away.

Directions

- adults and children 2 years of age and older:
- brush teeth thoroughly preferably after each meal or at least twice a day, or as directed by a dentist or doctor.
- Keep toothpaste in mouth for two to three minutes. Spit out and rinse with water.
- instruct children under 6 years of age in good brushing and rinsing habits (to minimize swallowing).
- supervise children as necessary until capable of using without supervision.
- children under 2 years of age: ask a dentist or doctor.

Other Information

- this product may produce surface staining of the teeth. Adequate tooth brushing may prevent these stains which are not harmful or permanent and may be removed by a dentist.
- this toothpaste contains natural herbs for maintaining oral health and nourishing gums. It may be used regularly everyday for oral care.
- green color results from natural chlorophyllin copper complex, and may turn darker over time.

Inactive ingredients

sorbitol, hydrated silica, water, PEG-8, sodium lauroyl sarcosinate, aroma, cellulose gum, zanthoxylum nitidum extract, clinopodium chinense extract, chlorophyllin-copper complex, chondrus crispus powder, titanium dioxide, ethyl menthane carboxamide, sodium saccharin, trisodium phosphate, sodium bicarbonate, benzyl alcohol, sodium chloride.

PACKAGE LABEL

DUAL-PURPOSE FOR MORE EFFECTIVE CARE

+ Stannous Fluoride Controls Gum Bleeding

+ Natural Herbs Maintain Healthy Gums and Teeth

PACKAGE LABEL

Refeshing Spearmint Flavor

NDC 71775-050-42

NET WT. 4.25 OZ (120g)

OTC with Herbs

INTRODUCING A NEW CONCEPT

that integrates the proven power of conventional fluoride toothpaste with natural Chinese herbs for superior oral care. Dr. Gingiva combines stannous fluoride, which controls gum bleeding, removes plaque, and prevents gingivitis and dental cavities, with natural Chinese herbs to maintain healthy teeth and gums. This dual-purpose formula is more effective in stopping bleeding and supporting oral health.

Designed and Distributed by:

Bad Students Inc

Product of China

PRINCIPAL DISPLAY PANEL

DR. GINGIVA

Anti-Gingivitis + Anti-Plaque + Anti-Cavity

CONTROLS GUM BLEEDING

Fluoride Toothpaste with Natural Herbs